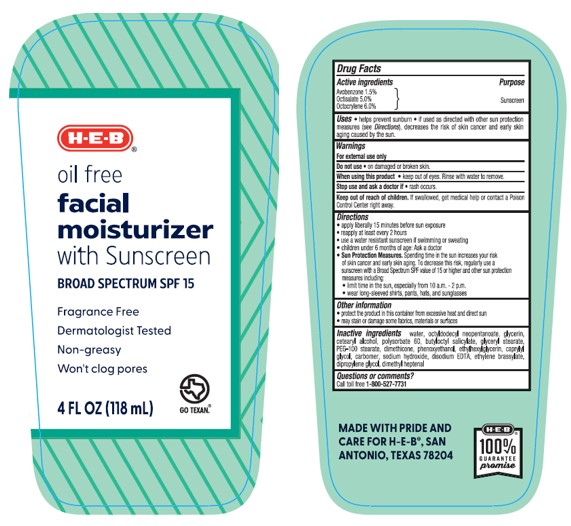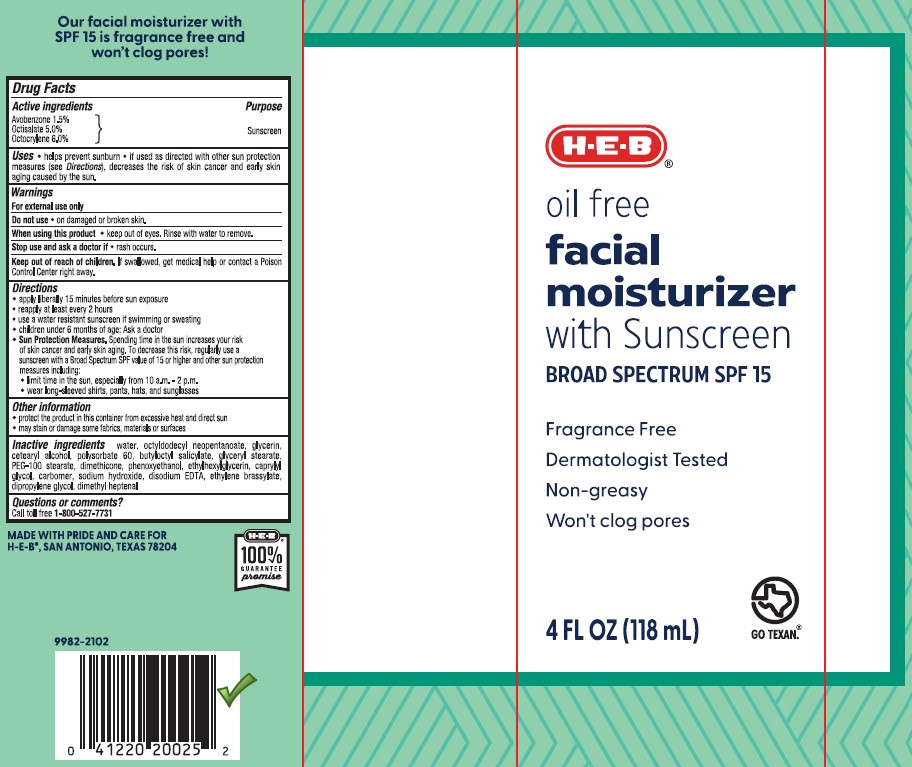 DRUG LABEL: HEB Oil Free Facial Moisturizer with Sunscreen Broad Spectrum SPF 15
NDC: 37808-129 | Form: LOTION
Manufacturer: H.E.B
Category: otc | Type: HUMAN OTC DRUG LABEL
Date: 20241015

ACTIVE INGREDIENTS: AVOBENZONE 15 mg/1 mL; OCTISALATE 50 mg/1 mL; OCTOCRYLENE 60 mg/1 mL
INACTIVE INGREDIENTS: WATER; GLYCERIN; EDETATE DISODIUM; CETOSTEARYL ALCOHOL; PHENOXYETHANOL; CAPRYLYL GLYCOL; SODIUM HYDROXIDE; ETHYLENE BRASSYLATE; PEG-100 STEARATE; HEXAMETHYLDISILOXANE; CARBOMER INTERPOLYMER TYPE A (ALLYL SUCROSE CROSSLINKED); BUTYLOCTYL SALICYLATE; OCTYLDODECYL NEOPENTANOATE; POLYSORBATE 60; GLYCERYL 1-STEARATE; 2,6-DIMETHYL-5-HEPTENAL; ETHYLHEXYLGLYCERIN; DIPROPYLENE GLYCOL

HEB Oil Free Facial Moisturizer with Sunscreen Broad Spectrum SPF 15

Active ingredients

Avobenzone 1.5%, Octisalate 5.0%, Octocrylene 6.0%

Purpose

Sunscreen

Uses

- helps prevent sunburn
- if used as directed with other sun protection measures (see Directions), decreases the risk of skin cancer and early skin aging caused by the sun

Warnings

For external use only

Do not use

• on damaged or broken skin.

When using this product

• keep out of eyes. Rinse with water to remove.

Stop use and ask a doctor if

• rash occurs.

Keep out of reach of children.

If swallowed, get medical help or contact a Poison Control Center right away.

Directions

- apply liberally 15 minutes before sun exposure
- use a water resistant sunscreen if swimming or sweating
- reapply at least every 2 hours
- children under 6 months of age: Ask a doctor
- Sun Protection Measures. Spending time in the sun increases your risk of skin cancer and early skin aging. To decrease this risk, regularly use a sunscreen with a Broad Spectrum SPF value of 15 or higher and other sun protection measures including:

• limit time in the sun, especially from 10 a.m. - 2 p.m.

• wear long-sleeved shirts, pants, hats, and sunglasses

Other information

- protect the product in this container from excessive heat and direct sun
- may stain or damage some fabrics, materials or surfaces

Inactive ingredients

water, octyldodecyl neopentanoate, glycerin, cetearyl alcohol, polysorbate 60, butyloctyl salicylate, glyceryl stearate, PEG-100 stearate, dimethicone, phenoxyethanol, ethylhexylglycerin, caprylyl glycol, carbomer, sodium hydroxide, disodium EDTA, ethylene brassylate, dipropylene glycol, dimethyl heptenal